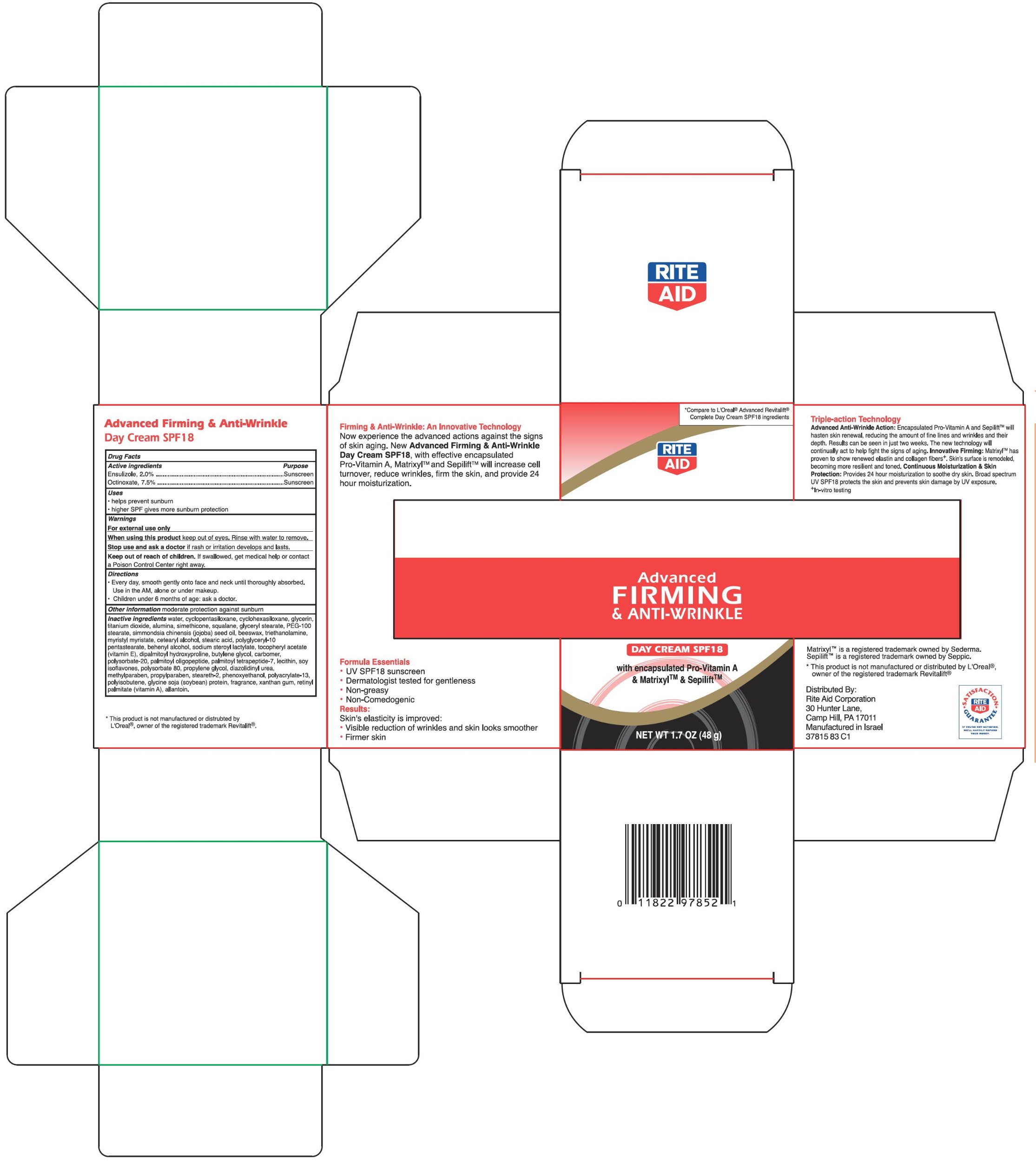 DRUG LABEL: Advanced Firming and Anti Wrinkle
NDC: 11822-0378 | Form: CREAM
Manufacturer: Rite Aid Corporation
Category: otc | Type: HUMAN OTC DRUG LABEL
Date: 20110226

ACTIVE INGREDIENTS: OCTINOXATE 7.5 g/100 g; ENSULIZOLE 2 g/100 g
INACTIVE INGREDIENTS: WATER; CYCLOMETHICONE 5; CYCLOMETHICONE 6; GLYCERIN; TITANIUM DIOXIDE; ALUMINUM OXIDE; SQUALANE; GLYCERYL MONOSTEARATE; PEG-100 STEARATE; YELLOW WAX; TROLAMINE; MYRISTYL MYRISTATE; CETOSTEARYL ALCOHOL; STEARIC ACID; DOCOSANOL; DIPALMITOYL HYDROXYPROLINE; BUTYLENE GLYCOL; PALMITOYL OLIGOPEPTIDE; PALMITOYL TETRAPEPTIDE-7; SOY ISOFLAVONES; POLYSORBATE 80; PROPYLENE GLYCOL; DIAZOLIDINYL UREA; METHYLPARABEN; PROPYLPARABEN; STEARETH-2; PHENOXYETHANOL; XANTHAN GUM; ALLANTOIN

Rite Aid Corporation Advanced Firming & Anti-Wrinkle Cream Drug Facts

Active ingredient

Ensulizole, 2.0%

Octinoxate, 7.5%

Purpose

Sunscreen

Uses

- helps prevent sunburn
- higher SPF gives more sunburn protection

Warnings

For external use only

When using this product

keep out of eyes. Rinse with water to remove.

Stop use and ask a doctor

if rash or irritation develops and lasts.

Keep out of reach of children.

If swallowed, get medical help or contact a Poison Control Center right away.

Directions

- Every day, smooth gently onto face and neck until thoroughly absorbed. Use in the AM, alone or under makeup.
- Children under 6 months of age: ask a doctor.

Other information

Moderate protection against sunburn

Inactive ingredients

water, cyclopentasiloxane, cyclohexasiloxane, glycerin, titanium dioxide, alumina, simethicone, squalane, glyceryl stearate, PEG-100 stearate, simmondsia chinensis (jojoba) seed oil, beeswax, triethanolamine, myristyl myristate, cetearyl alcohol, stearic acid, polyglyceryl-10 pentastearate, behenyl alcohol, sodium steroyl lactylate, tocopheryl acetate (vitamin E), dipalmitoyl hydroxyproline, butylene glycol, carbomer, polysorbate-20, palmitoyl oligopeptide, palmitoyl tetrapeptide-7, lecithin, soy isoflavones, polysorbate 80, propylene glycol, diazolidinyl urea, methylparaben, propylparaben, steareth-2, phenoxyethanol, polyacrylate-13, polyisobutene, glycine soja (soybean) protein, fragrance, xanthan gum, retinyl palmitate (vitamin A), allantoin.

Principal Display Panel

Compare to L'Oreal® Advanced Revitalift® Complete Day Cream SPF18 ingredients

Advanced Firming & Anti-Wrinkle

Day Cream SPF 18

with encapsulated Pro-Vitamin A & Matrixyl™ & Sepilift™

Advanced Firming & Anti-Wrinkle Cream Carton